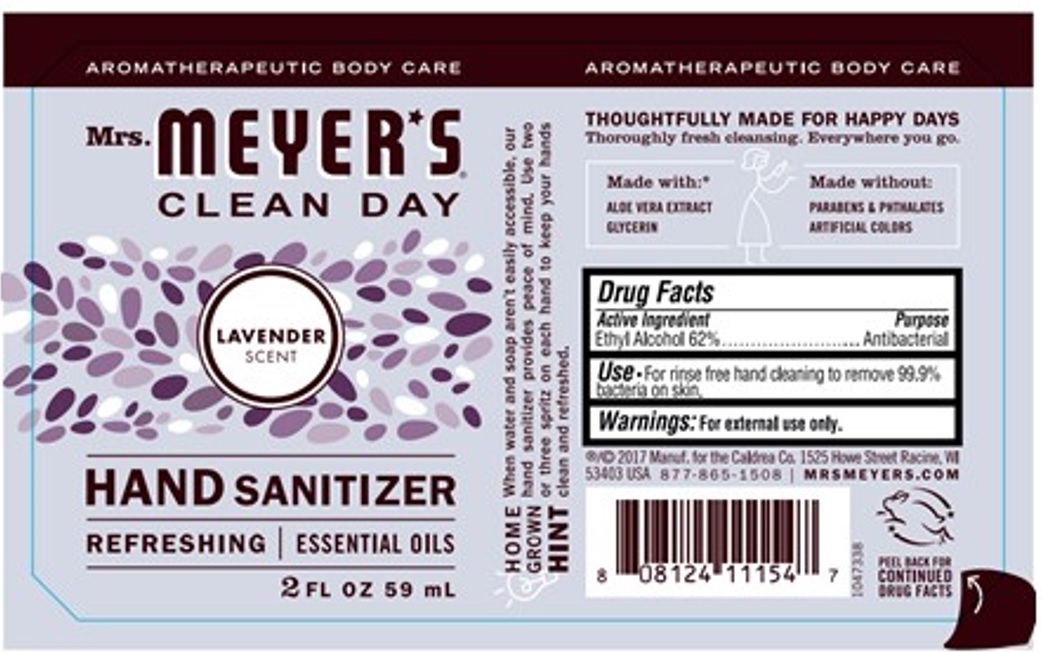 DRUG LABEL: Mrs. Meyers Hand Sanitizer Lavender Scent
NDC: 68534-001 | Form: LIQUID
Manufacturer: METROPOLITANGRAPHIC ARTS, Inc.
Category: otc | Type: HUMAN OTC DRUG LABEL
Date: 20251021

ACTIVE INGREDIENTS: ALCOHOL 62 mL/100 mL
INACTIVE INGREDIENTS: GLYCERIN; WATER; ALOE VERA LEAF; LAVENDER OIL; ORANGE OIL, COLD PRESSED; LINALOOL, (+/-)-; GERANIOL; GERANYL ACETATE; COUMARIN; PHENYLETHYL ALCOHOL; ANISYL ACETATE; HEXYL SALICYLATE; LIMONENE, (+)-; LAVANDIN OIL; DIPROPYLENE GLYCOL

Active ingredient

Ethyl Alcohol 62%

Purpose

Antibacterial

Uses

For rinse free hand cleaning to remove 99.9% bacteria on skin

Warning

For external use only. Eye and Skin Irritation, Flammable Liquid & Vapor

Direction

Skin and Eye Care, Handling & Storage

Inactive ingredients

Water, glycerin, Aloe barbadensis leaf juice, Lavandula Angustifolia (Lavender) oil, Citrus Aurantium Dulcis (Orange) peel oil, [ Fragrance: Linalool, geraniol, geranyl acetate, coumarin, phenethyl alcohol, p-methoxybenzyl acetate, hexyl salicylate, limonene, lavandula hybrida oil, dipropylene glycol ]